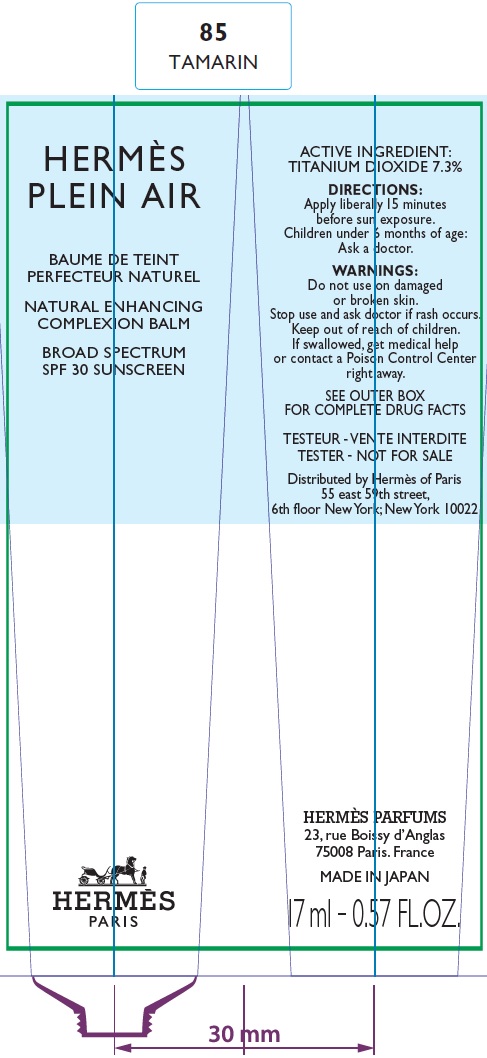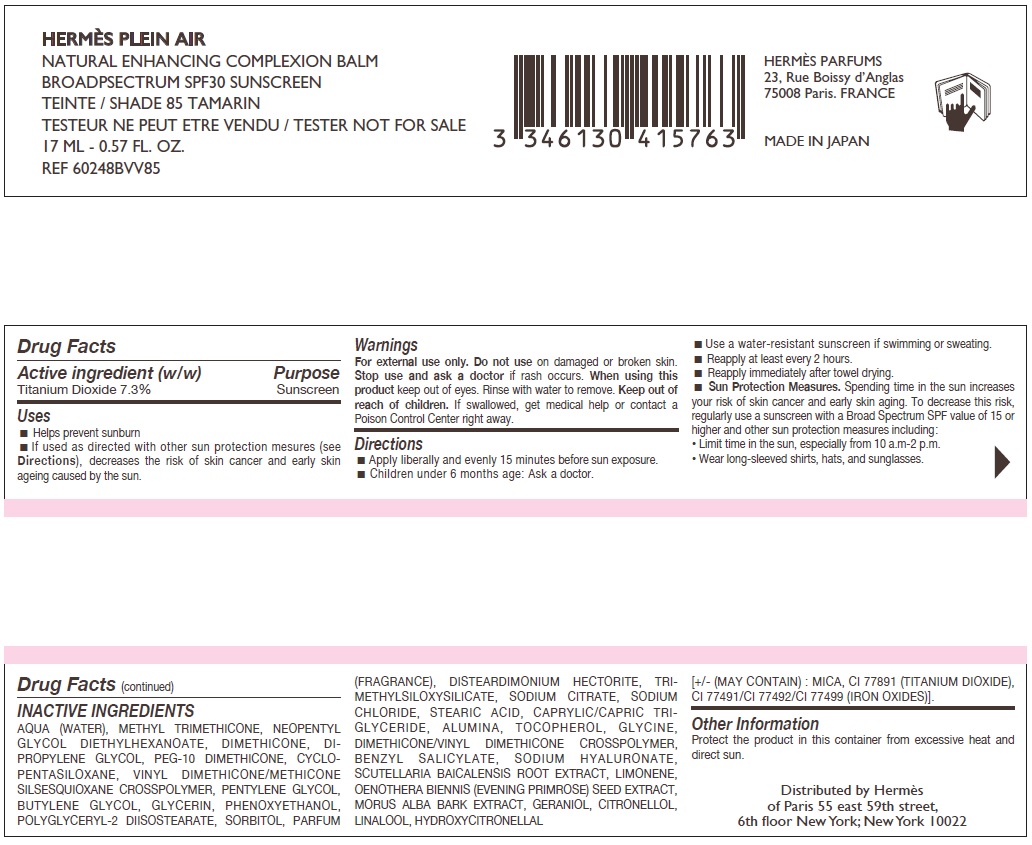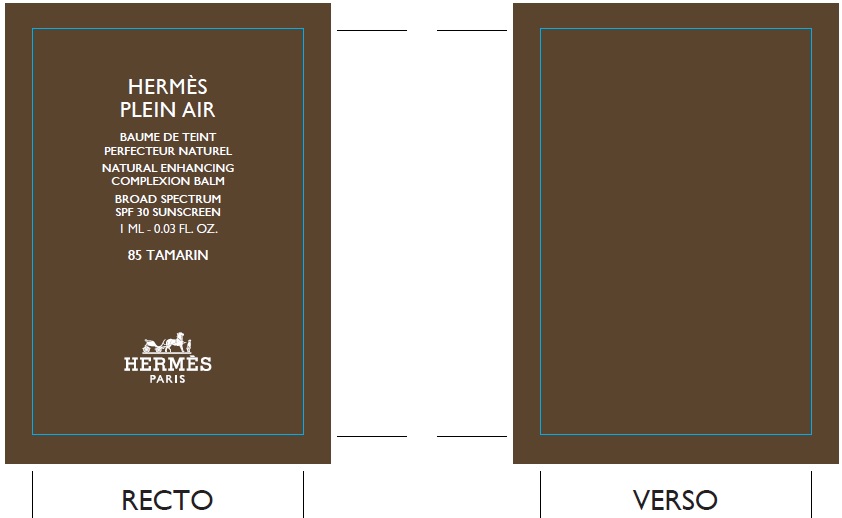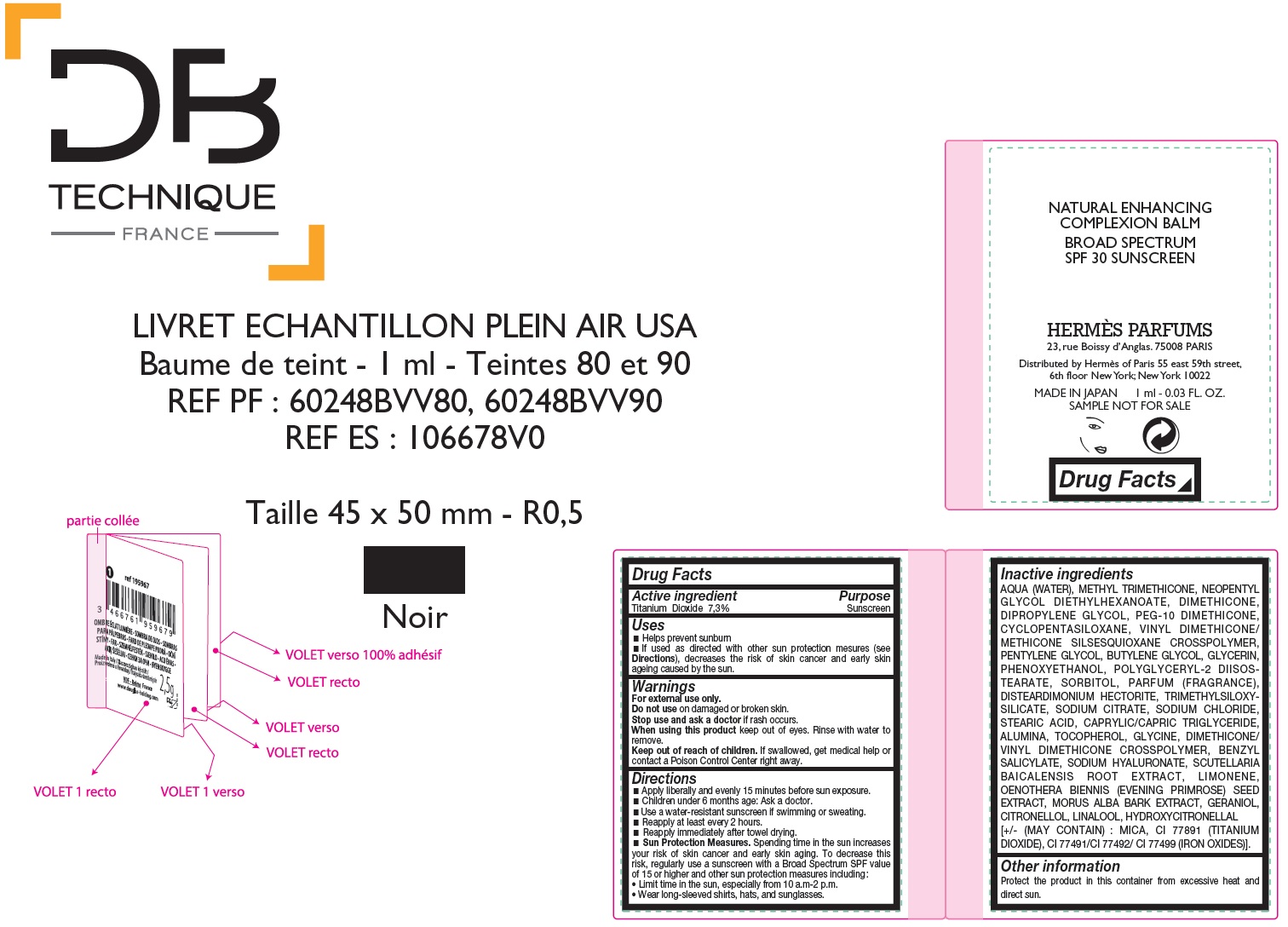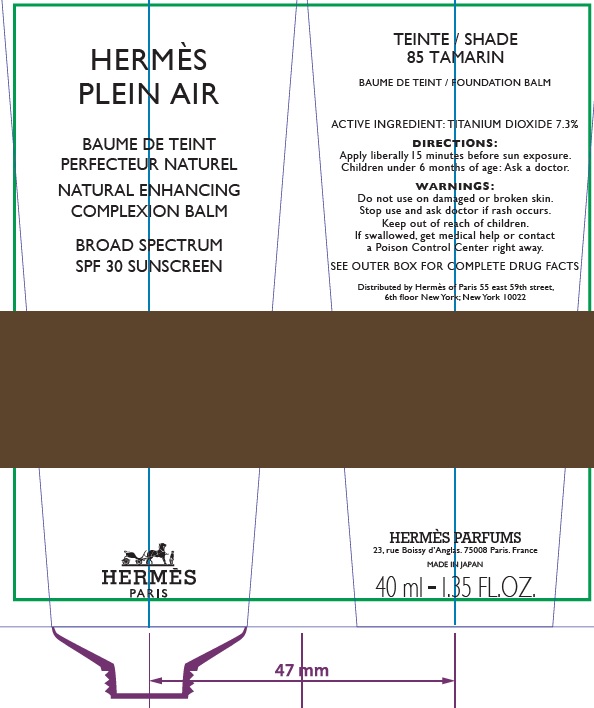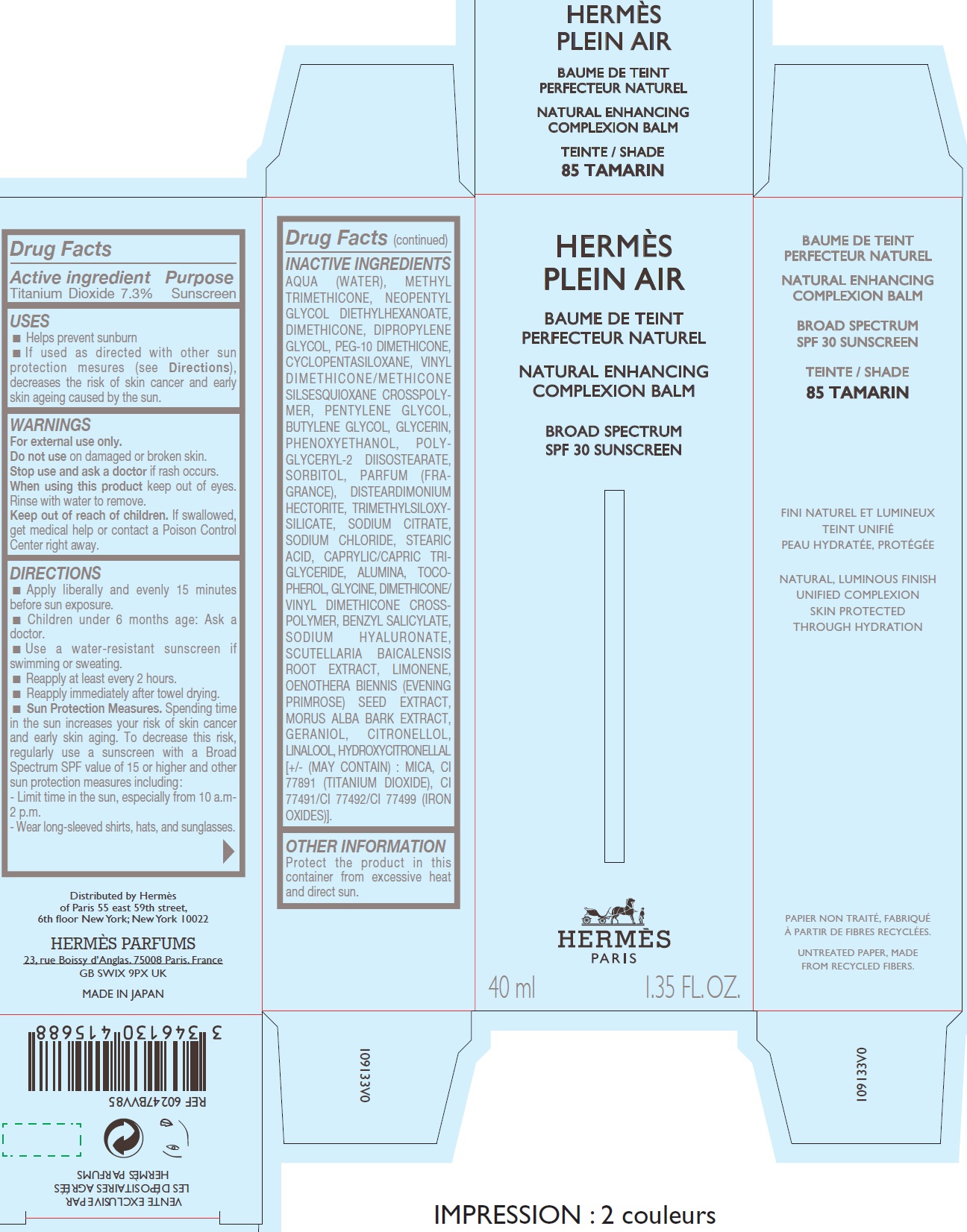 DRUG LABEL: Hermes Plein Air-Baume de Teint Perfecteur Naturel-Enhancing Complexion Balm 85 TAMARIN
NDC: 82494-010 | Form: CREAM
Manufacturer: S.A. COMPTOIR NOUVEAU DE LA PARFUMERIE
Category: otc | Type: HUMAN OTC DRUG LABEL
Date: 20260218

ACTIVE INGREDIENTS: TITANIUM DIOXIDE 73 mg/1 mL
INACTIVE INGREDIENTS: WATER; METHYL TRIMETHICONE; NEOPENTYL GLYCOL DIETHYLHEXANOATE; DIMETHICONE; DIPROPYLENE GLYCOL; CYCLOMETHICONE 5; VINYL DIMETHICONE/METHICONE SILSESQUIOXANE CROSSPOLYMER; PENTYLENE GLYCOL; BUTYLENE GLYCOL; GLYCERIN; PHENOXYETHANOL; POLYGLYCERYL-2 DIISOSTEARATE; SORBITOL; DISTEARDIMONIUM HECTORITE; SODIUM CITRATE; SODIUM CHLORIDE; STEARIC ACID; MEDIUM-CHAIN TRIGLYCERIDES; ALUMINUM OXIDE; TOCOPHEROL; GLYCINE; BENZYL SALICYLATE; HYALURONATE SODIUM; SCUTELLARIA BAICALENSIS ROOT; LIMONENE, (+)-; EVENING PRIMROSE OIL; MORUS ALBA BARK; GERANIOL; .BETA.-CITRONELLOL, (R)-; LINALOOL, (+/-)-; HYDROXYCITRONELLAL

Hermes Plein Air-Baume de Teint Perfecteur Naturel-Enhancing Complexion Balm 85 TAMARIN

Active ingredient

Titanium Dioxide 7,3%

Purpose

Sunscreen

Uses

- Helps prevent sunburn
- If used as directed with other sun protection mesures (see), decreases the risk of skin cancer and early skin ageing caused by the sun. Directions

Warnings

For external use only.

Do not use

on damaged or broken skin.

Stop use and ask a doctor

if rash occurs.

When using this product

keep out of eyes. Rinse with water to remove.

Keep out of reach of children.

If swallowed, get medical help or contact a Poison Control Center right away.

Directions

- Apply liberally and evenly 15 minutes before sun exposure.
- Children under 6 months age: Ask a doctor.
- Use a water-resistant sunscreen if swimming or sweating.
- Reapply at least every 2 hours.
- Reapply immediately after towel drying.
- Spending time in the sun increases your risk of skin cancer and early skin aging. To decrease this risk, regularly use a sunscreen with a Broad Spectrum SPF value of 15 or higher and other sun protection measures including : Sun Protection Measures.
- Limit time in the sun, especially from 10 a.m-2 p.m.
- Wear long-sleeved shirts, hats, and sunglasses.

Inactive ingredients

AQUA (WATER), METHYL TRIMETHICONE, NEOPENTYL GLYCOL DIETHYLHEXANOATE, DIMETHICONE, DIPROPYLENE GLYCOL, PEG-10 DIMETHICONE, CYCLOPENTASILOXANE, VINYL DIMETHICONE/ METHICONE SILSESQUIOXANE CROSSPOLYMER, PENTYLENE GLYCOL, BUTYLENE GLYCOL, GLYCERIN, PHENOXYETHANOL, POLYGLYCERYL-2 DIISOSTEARATE, SORBITOL, PARFUM (FRAGRANCE), DISTEARDIMONIUM HECTORITE, TRIMETHYLSILOXYSILICATE, SODIUM CITRATE, SODIUM CHLORIDE, STEARIC ACID, CAPRYLIC/CAPRIC TRIGLYCERIDE, ALUMINA, TOCOPHEROL, GLYCINE, DIMETHICONE/ VINYL DIMETHICONE CROSSPOLYMER, BENZYL SALICYLATE, SODIUM HYALURONATE, SCUTELLARIA BAICALENSIS ROOT EXTRACT, LIMONENE, OENOTHERA BIENNIS (EVENING PRIMROSE) SEED EXTRACT, MORUS ALBA BARK EXTRACT, GERANIOL, CITRONELLOL, LINALOOL, HYDROXYCITRONELLAL [+/- (MAY CONTAIN) : MICA, CI 77891 (TITANIUM DIOXIDE), CI 77491/CI 77492/ CI 77499 (IRON OXIDES)].

Other information

Protect the product in this container from excessive heat and direct sun.